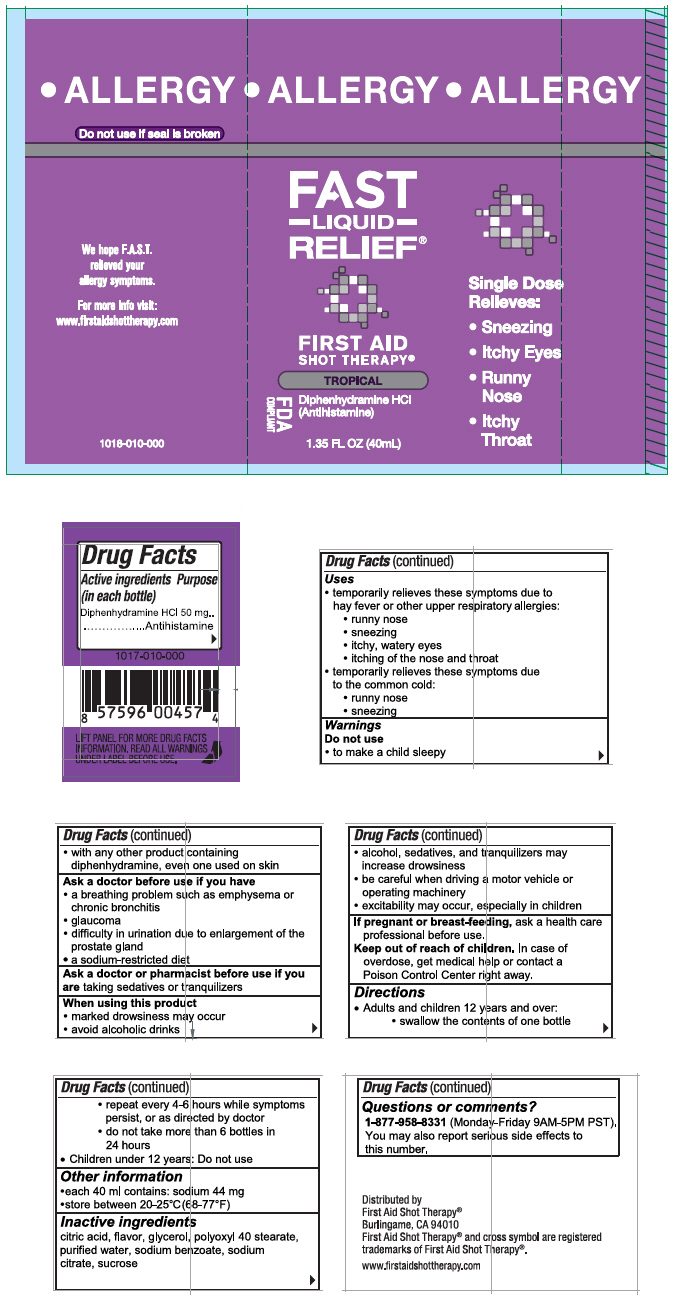 DRUG LABEL: First Aid Shot Therapy Allergy Relief
NDC: 57815-010 | Form: SOLUTION
Manufacturer: First Aid Beverages, Inc.
Category: otc | Type: HUMAN OTC DRUG LABEL
Date: 20160620

ACTIVE INGREDIENTS: Diphenhydramine Hydrochloride 50 mg/40 mL
INACTIVE INGREDIENTS: POLYOXYL 40 STEARATE; GLYCERIN; TRISODIUM CITRATE DIHYDRATE; ANHYDROUS CITRIC ACID; SODIUM BENZOATE; SUCROSE; WATER

First Aid Shot Therapy® Allergy Relief®

Drug Facts

Active ingredient

Diphenhydramine HCl 50 mg

Purpose (in each bottle)

Antihistamine

Uses

- temporarily relieves these symptoms due to hay fever or other upper respiratory allergies:
  - runny nose
  - sneezing
  - itchy, watery eyes
  - itching of the nose and throat
- temporarily relieves these symptoms due to the common cold:
  - runny nose
  - sneezing

Warnings

Do not use

- to make a child sleepy
- with any other product containing diphenhydramine, even one used on skin

Ask a doctor before use if you have

- a breathing problem such as emphysema or chronic bronchitis
- glaucoma
- difficulty in urination due to enlargement of the prostate gland
- a sodium-restricted diet

Ask a doctor or pharmacist before use if you are taking sedatives or tranquilizers

When using this product

- marked drowsiness may occur
- avoid alcoholic drinks
- alcohol, sedatives, and tranquilizers may increase drowsiness
- be careful when driving a motor vehicle or operating machinery
- excitability may occur, especially in children

PREGNANCY OR BREAST FEEDING

If pregnant or breast-feeding, ask a health care professional before use.

Keep out of reach of children. In case of overdose, get medical help or contact a Poison Control Center right away.

Directions

- Adults and children 12 years and over:
  - swallow the contents of one bottle
  - repeat every 4-6 hours while symptoms persist, or as directed by doctor
  - do not take more than 6 bottles in 24 hours
- Children under 12 years: Do not use

Other information

- each 40 ml contains: sodium 44 mg
- store between 20-25C°(68-77°F)

Inactive ingredients

citric acid, flavor, glycerol, polyoxyl 40 stearate, purified water, sodium benzoate, sodium citrate, sucrose

Questions or comments?

1-877-958-8331 (Monday-Friday 9AM-5PM PST). You may also report serious side effects to this number.

Distributed by
First Aid Shot Therapy®
Burlingame, CA 94010

PRINCIPAL DISPLAY PANEL - 40mL Bottle Label

ALLERGY

FAST
–LIQUID–
RELIEF®

FIRST AID
SHOT THERAPY®

TROPICAL

FDA
COMPLIANT

Diphenhydramine HCl
(Antihistamine)

1.35 FL OZ (40mL)